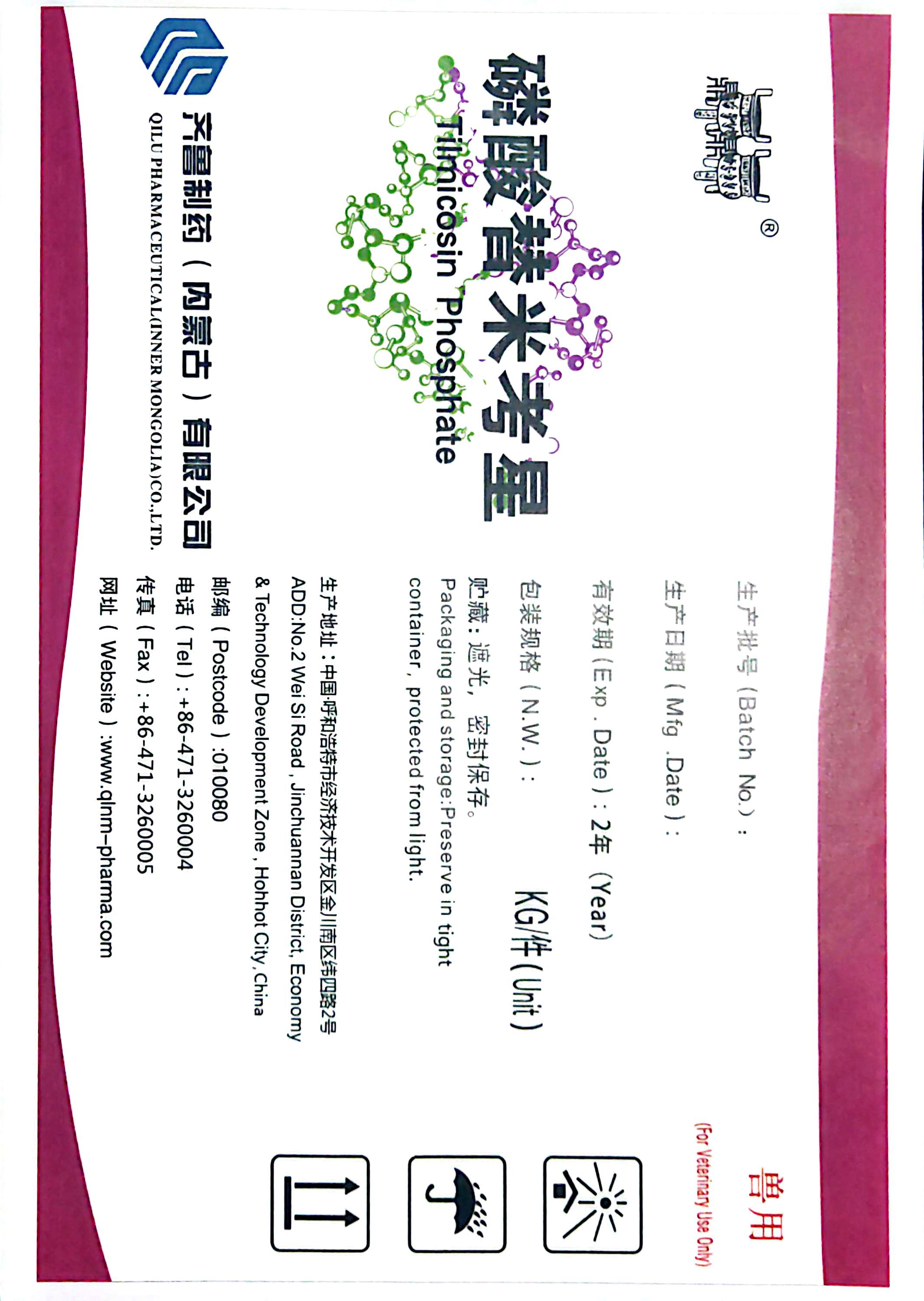 DRUG LABEL: Tilmicosin Phosphate
NDC: 86098-0004 | Form: POWDER
Manufacturer: Qilu Pharmaceutical (Inner Mongolia) Co., Ltd.
Category: other | Type: BULK INGREDIENT - ANIMAL DRUG
Date: 20251121

ACTIVE INGREDIENTS: TILMICOSIN PHOSPHATE 15 kg/15 kg

Tilmicosin Phosphate

PACKAGE LABEL

Tilmicosin Phosphate
QILU PHARMACEUTICAL (INNER MONGOLIA) CO.,LTD.
ADD:No.2 Wei Si Road, Jinchuannan District, Economy &Technology Development Zone, Hohhot City, China
Batch No.:
Mfg.Date:
Exp.Date: 2 (Year)
N.W.: KG/Unit
Packaging and storage: Preserve in tight container, protected from light.
Postcode:010080
Tel:+86-471-3260004
Fax:+86-471-3260005
Website: www.qlnm-pharma.com